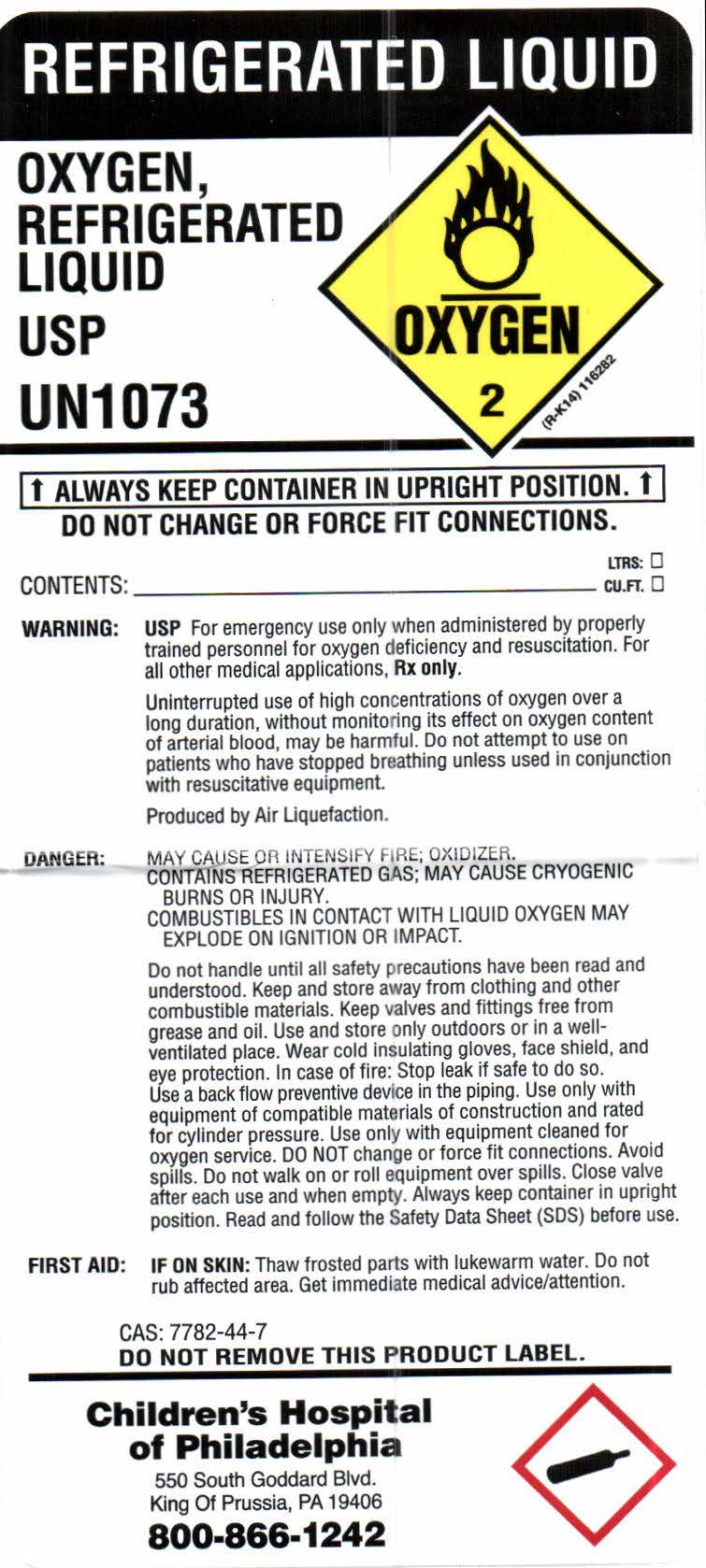 DRUG LABEL: OXYGEN
NDC: 43734-002 | Form: GAS
Manufacturer: Childrens Hospital of Philadelphia
Category: prescription | Type: HUMAN PRESCRIPTION DRUG LABEL
Date: 20211230

ACTIVE INGREDIENTS: OXYGEN 99 L/100 L

OXYGEN REFRIGERATED LIQUIP USP

OXYGEN REFRIGERATED LIQUID USP product label

REFRIGERATED LIQUID

OXYGEN, REFRIGERATED LIQUID USP

UN 1073

OXYGEN 2 (R-K14) 116282

↑ ALWAYS KEEP CONTAINER IN UPRIGHT POSITION. ↑

DO NOT CHANGE OR FORCE FIT CONNECTIONS.

CONTENTS: ____________________ LTRS. CU.FT.

WARNING: USP For emergency use only when administered by properly trained personnel for oxygen deficiency and resuscitation. For other medical applications, Rx only.

Uninterrupted use of high concentrations of oxygen over a long duration, without onitoring its effect on oxygen content of arterial blood, may be harmful. Do not attempt to use on patients who have stopped breathing unless used in conjunction with resuscitative equipment.

Produced by Air Liquefaction.

DANGER: MAY CAUSE OR INTENSIFY FIRE; OXIDIZZER. CONTAINS REFRIGERATED GAS; MAY CAUSE CRYOGENIC BURNS OR INJURY. COMBUSTIBLES IN CONTACT WITH LIQUID OXYGEN MAY EXPLODE ON IGNITION OR IMPACT.

Do not handle until all safety precautions have been read and understood. Keep and store away from clothing and other combustible materials. Keep valves and fittings free from grease and oil. Use and store only outdoors or in a well-ventilated place. Wear cold insulating gloves, face shield, and eye protection. In case of fire: Stop leak if safe to do so. Use a back flow preventive device in the piping. Use only with equipment of compatible materials of construction and rated for cylinder pressure. Use only with equipment cleaned for oxygen service. DO NOT change or force fit connections. Avoid spills. Do not walk or roll equipment over spills. Close valve after each use and when empty. Always keep container in upright position. Read and follow the Safety Data Sheet (SDS) before use.

FIRST AID: IF ON SKIN: Thaw frosted parts with lukewarm water. Do not rub affected area. Get immediate medical advise/attention.

CAS: 7782-44-7

DO NOT REMOVE THIS LABEL.

Children's Hospital of Philadelphia

550 South Goddard Blvd.

King of Prussia, PA 19406

800-866-1242